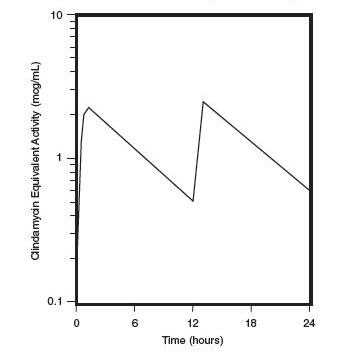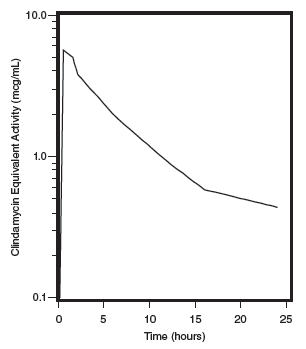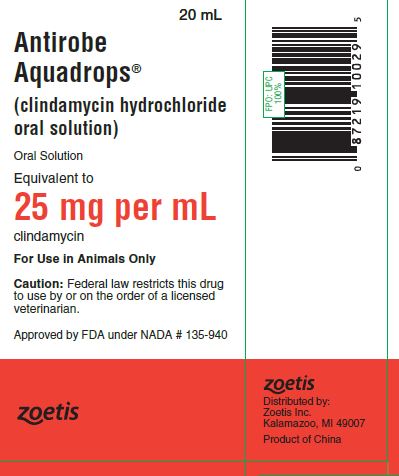 DRUG LABEL: Antirobe Aquadrops
NDC: 54771-3179 | Form: LIQUID
Manufacturer: Zoetis Inc.
Category: animal | Type: PRESCRIPTION ANIMAL DRUG LABEL
Date: 20230331

ACTIVE INGREDIENTS: CLINDAMYCIN HYDROCHLORIDE 25 mg/1 mL
INACTIVE INGREDIENTS: ALCOHOL 0.0864 mL/1 mL

Antirobe Aquadrops®

Antirobe Aquadrops® brand of clindamycin hydrochloride oral solution

Caution

Federal law restricts this drug to use by or on the order of a licensed veterinarian.

DESCRIPTION

ANTIROBE Capsules and ANTIROBE AQUADROPS Liquid contain clindamycin hydrochloride which is the hydrated salt of clindamycin. Clindamycin is a semisynthetic antibiotic produced by a 7(S)-chlorosubstitution of the 7(R)-hydroxyl group of a naturally produced antibiotic produced by Streptomyces lincolnensis var. lincolnensis.

ANTIROBE Capsules (For Use in Dogs Only):

25 mg Capsule, each yellow and white capsule contains clindamycin hydrochloride equivalent to 25 mg of clindamycin.

75 mg Capsule, each green capsule contains clindamycin hydrochloride equivalent to 75 mg of clindamycin.

150 mg Capsule, each light blue and green capsule contains clindamycin hydrochloride equivalent to 150 mg of clindamycin.

ANTIROBE AQUADROPS Liquid (For Use in Dogs and Cats) is a palatable formulation intended for oral administration. Each mL of ANTIROBE AQUADROPS Liquid contains clindamycin hydrochloride equivalent to 25 mg clindamycin; and ethyl alcohol, 7.4%.

ACTIONS

Site and Mode of Action

Clindamycin is an inhibitor of protein synthesis in the bacterial cell. The site of binding appears to be in the 5OS sub-unit of the ribosome. Binding occurs to the soluble RNA fraction of certain ribosomes, thereby inhibiting the binding of amino acids to those ribosomes. Clindamycin differs from cell wall inhibitors in that it causes irreversible modification of the protein-synthesizing subcellular elements at the ribosomal level.

MICROBIOLOGY

Clindamycin is a lincosaminide antimicrobial agent with activity against a wide variety of aerobic and anaerobic bacterial pathogens. Clindamycin is a bacteriostatic compound that inhibits bacterial protein synthesis by binding to the 5OS ribosomal sub-unit. The minimum inhibitory concentrations (MICs) of Gram-positive and obligate anaerobic pathogens isolated from dogs and cats in the United States are presented in Table 1 and Table 2. Bacteria were isolated in 1998-1999. All MICs were performed in accordance with the National Committee for Clinical Laboratory Standards (NCCLS).

Table 1. Clindamycin MIC Values (μg/mL) from Diagnostic Laboratory Survey Data Evaluating Canine Pathogens in the U.S. during 1998-99 [The correlation between the in vitro susceptibility data and clinical response has not been determined.]
Organism | Number of Isolates | MIC50 | MIC85 | MIC90 | Range
Soft Tissue/Wound [Soft Tissue/Wound: includes samples labeled wound, abscess, aspirate, exudates, draining tract, lesion, and mass]
Staphylococcus aureus | 17 | 0.5 | 0.5 | ≥4.0 | 0.25-≥4.0
Staphylococcus intermedius | 28 | 0.25 | 0.5 | ≥4.0 | 0.125-≥4.0
Staphylococcus spp. | 18 | 0.5 | 0.5 | ≥4.0 | 0.25-≥4.0
Beta-hemolytic streptococci | 46 | 0.5 | 0.5 | ≥4.0 | 0.25-≥4.0
Streptococcus spp. | 11 | 0.5 | ≥4.0 | ≥4.0 | 0.25-≥4.0
Osteomyelitis/Bone [Osteomyelitis/Bone: includes samples labeled bone, fracture, joint, tendon]
Staphylococcus aureus | 20 | 0.5 | 0.5 | 0.5 | 0.5 [No range, all isolates yielded the same value]
Staphylococcus intermedius | 15 | 0.5 | ≥4.0 | ≥4.0 | 0.25-≥4.0
Staphylococcus spp. | 18 | 0.5 | ≥4.0 | ≥4.0 | 0.25-≥4.0
Beta-hemolytic streptococci | 21 | 0.5 | 2.0 | 2.0 | 0.25-≥4.0
Streptococcus spp. | 21 | ≥4.0 | ≥4.0 | ≥4.0 | 0.25-≥4.0
Dermal/Skin [Dermal/Skin: includes samples labeled skin, skin swab, biopsy, incision, lip]
Staphylococcus aureus | 25 | 0.5 | ≥4.0 | ≥4.0 | 0.25-≥4.0
Staphylococcus intermedius | 48 | 0.5 | ≥4.0 | ≥4.0 | 0.125-≥4.0
Staphylococcus spp. | 32 | 0.5 | ≥4.0 | ≥4.0 | 0.25-≥4.0
Beta-hemolytic streptococci | 17 | 0.5 | 0.5 | 0.5 | 0.25-0.5

Table 2. Clindamycin MIC Values (μg/mL) from Diagnostic Laboratory Survey Data Evaluating Feline Pathogens from Wound and Abscess Samples in the U.S. during 1998 [The correlation between the in vitro susceptibility data and clinical response has not been determined.]
Organism | Number of Isolates | MIC50 | MIC90 | Range
Bacteroides/Prevotella | 30 | 0.06 | 4.0 | ≤0.015-4.0
Fusobacterium spp. | 17 | 0.25 | 0.25 | ≤0.015-0.5
Peptostreptococcus spp. | 18 | 0.13 | 0.5 | ≤0.015-8.0
Porphyromonas spp. | 13 | 0.06 | 0.25 | ≤0.015-8.0

PHARMACOLOGY

Absorption

Clindamycin hydrochloride is rapidly absorbed from the canine and feline gastrointestinal tract.

Dog Serum Levels

Serum levels at or above 0.5 μg/mL can be maintained by oral dosing at a rate of 2.5 mg/lb of clindamycin hydrochloride every 12 hours. This same study revealed that average peak serum concentrations of clindamycin occur 1 hour and 15 minutes after oral dosing. The elimination half-life for clindamycin in dog serum was approximately 5 hours. There was no bioactivity accumulation after a regimen of multiple oral doses in healthy dogs.

Clindamycin Serum Concentrations 2.5 mg/lb (5.5 mg/kg) After B.I.D. Oral Dose of Antirobe Capsules to Dogs

Cat Serum Levels

Serum levels at or above 0.5 μg/mL can be maintained by oral dosing at a rate of 5 mg/lb of clindamycin hydrochloride liquid every 24 hours. The average peak serum concentration of clindamycin occurs approximately 1 hour after oral dosing. The elimination half-life of clindamycin in feline serum is approximately 7.5 hours. In healthy cats, minimal accumulation occurs after multiple oral doses of clindamycin hydrochloride, and steady-state should be achieved by the third dose.

Clindamycin Serum Concentrations 5 mg/lb (11 mg/kg) After Single Oral Dose of Antirobe Aquadrops to Cats

METABOLISM AND EXCRETION

Extensive studies of the metabolism and excretion of clindamycin hydrochloride administered orally in animals and humans have shown that unchanged drug and bioactive and bioinactive metabolites are excreted in urine and feces. Almost all of the bioactivity detected in serum after ANTIROBE product administration is due to the parent molecule (clindamycin). Urine bioactivity, however, reflects a mixture of clindamycin and active metabolites, especially N-demethyl clindamycin and clindamycin sulfoxide.

ANIMAL SAFETY SUMMARY

Rat and Dog Data

One year oral toxicity studies in rats and dogs at doses of 30, 100 and 300 mg/kg/day (13.6, 45.5 and 136.4 mg/lb/day) have shown clindamycin hydrochloride capsules to be well tolerated. Differences did not occur in the parameters evaluated to assess toxicity when comparing groups of treated animals with contemporary controls. Rats administered clindamycin hydrochloride at 600 mg/kg/day (272.7 mg/lb/day) for six months tolerated the drug well; however, dogs orally dosed at 600 mg/kg/day (272.7 mg/lb/day) vomited, had anorexia, and subsequently lost weight. At necropsy these dogs had erosive gastritis and focal areas of necrosis of the mucosa of the gallbladder.

Safety in gestating bitches or breeding males has not been established.

Cat Data

The recommended daily therapeutic dose range for clindamycin hydrochloride (ANTIROBE AQUADROPS oral solution) is 11 to 33 mg/kg/day (5 to 15 mg/lb/day) depending on the severity of the condition. Clindamycin hydrochloride (ANTIROBE AQUADROPS oral soluation) was tolerated with little evidence of toxicity in domestic shorthair cats when administered orally at 10× the minimum recommended therapeutic daily dose (11 mg/kg; 5 mg/lb) for 15 days, and at doses up to 5× the minimum recommended therapeutic dose for 42 days. Gastrointestinal tract upset (soft feces to diarrhea) occurred in control and treated cats with emesis occurring at doses 3× or greater than the minimum recommended therapeutic dose (11 mg/kg/day; 5 mg/lb/day). Lymphocytic inflammation of the gallbladder was noted in a greater number of treated cats at the 110 mg/kg/day (50 mg/lb/day) dose level than for control cats. No other effects were noted. Safety in gestating queens or breeding male cats has not been established.

INDICATIONS

ANTIROBE (brand of clindamycin hydrochloride) Capsules (for use in dogs only) and AQUADROPS oral solution (for use in dogs and cats) are indicated for the treatment of infections caused by susceptible strains of the designated microorganisms in the specific conditions listed below:

Dogs: Skin infections (wounds and abscesses) due to coagulase positive staphylococci (Staphylococcus aureus or Staphylococcus intermedius). Deep wounds and abscesses due to Bacteroides fragilis, Prevotella melaninogenicus, Fusobacterium necrophorum and Clostridium perfringens. Dental infections due to Staphylococcus aureus, Bacteroides fragilis, Prevotella melaninogenicus, Fusobacterium necrophorum and Clostridium perfringens. Osteomyelitis due to Staphylococcus aureus, Bacteroides fragilis, Prevotella melaninogenicus, Fusobacterium necrophorum and Clostridium perfringens.

Cats: Skin infections (wounds and abscesses) due to Staphylococcus aureus, Staphylococcus intermedius, Streptococcus spp. Deep wounds and abscesses due to Clostridium perfringens and Bacteroides fragilis.

Dental infections due to Staphylococcus aureus, Staphylococcus intermedius, Streptococcus spp., Clostridium perfringens and Bacteroides fragilis.

CONTRAINDICATIONS

ANTIROBE Capsules and ANTIROBE AQUADROPS oral solution are contraindicated in animals with a history of hypersensitivity to preparations containing clindamycin or lincomycin.

Because of potential adverse gastrointestinal effects, do not administer to rabbits, hamsters, guinea pigs, horses, chinchillas or ruminating animals.

WARNINGS

Keep out of reach of children. Not for human use.

PRECAUTIONS

During prolonged therapy of one month or greater, periodic liver and kidney function tests and blood counts should be performed.

The use of ANTIROBE occasionally results in overgrowth of non-susceptible organisms such as clostridia and yeasts. Therefore, the administration of ANTIROBE should be avoided in those species sensitive to the gastrointestinal effects of clindamycin (see CONTRAINDICATIONS). Should superinfections occur, appropriate measures should be taken as indicated by the clinical situation.

Patients with very severe renal disease and/or very severe hepatic disease accompanied by severe metabolic aberrations should be dosed with caution, and serum clindamycin levels monitored during high-dose therapy.

Clindamycin hydrochloride has been shown to have neuromuscular blocking properties that may enhance the action of other neuromuscular blocking agents. Therefore, ANTIROBE should be used with caution in animals receiving such agents.

Safety in gestating bitches and queens or breeding male dogs and cats has not been established.

ADVERSE REACTIONS

Side effects occasionally observed in either clinical trials or during clinical use were vomiting and diarrhea.

To report adverse reactions or a suspected adverse reaction call 1-888-963-8471.

DOSAGE AND ADMINISTRATION

Dogs

Infected Wounds, Abscesses, and Dental Infections

Oral: 2.5-15.0 mg/lb body weight every 12 hours.

Duration: Treatment with ANTIROBE products may be continued up to a maximum of 28 days if clinical judgment indicates. Treatment of acute infections should not be continued for more than three or four days if no response to therapy is seen.

Dosage Schedule:

Capsules

ANTIROBE 25 mg, administer 1-6 capsules every 12 hours for each 10 pounds of body weight.

ANTIROBE 75 mg, administer 1-6 capsules every 12 hours for each 30 pounds of body weight.

ANTIROBE 150 mg, administer 1-6 capsules every 12 hours for each 60 pounds of body weight.

Oral Solution

ANTIROBE AQUADROPS, administer 1-6 mL/10 lbs body weight every 12 hours.

Dogs

Osteomyelitis

Oral: 5.0-15.0 mg/lb body weight every 12 hours

Duration: Treatment with ANTIROBE is recommended for a minimum of 28 days. Treatment should not be continued for longer than 28 days if no response to therapy is seen.

Dosage Schedule:

Capsules

ANTIROBE 25 mg, administer 2-6 capsules every 12 hours for each 10 pounds of body weight.

ANTIROBE 75 mg, administer 2-6 capsules every 12 hours for each 30 pounds of body weight.

ANTIROBE 150 mg, administer 2-6 capsules every 12 hours for each 60 pounds of body weight.

Oral Solution

ANTIROBE AQUADROPS, administer 2-6 mL/ 10 lbs body weight every 12 hours.

Cats

Infected Wounds, Abscesses, and Dental Infections

5.0 - 15.0 mg/lb body weight once every 24 hours depending on the severity of the condition.

Duration: Treatment with ANTIROBE AQUADROPS oral solution may be continued up to a maximum of 14 days if clinical judgment indicates. Treatment of acute infections should not be continued for more than three to four days if no clinical response to therapy is seen.

Dosage Schedule:

ANTIROBE AQUADROPS, to provide 5.0 mg/lb, administer 1 mL/5 lbs body weight once every 24 hours; to provide 15.0 mg/lb, administer 3 mL/5 lbs body weight once every 24 hours.

HOW SUPPLIED

ANTIROBE AQUADROPS oral solution is available as 20 mL filled in 30 mL bottles (25 mg/mL) supplied in packers containing 12 cartoned bottles with direction labels and calibrated dosing droppers.
Approved by FDA under NADA # 135-940
For a copy of the Safety Data Sheet (SDS) or to report adverse reactions call Zoetis Inc. at 1-888-963-8471. For additional information aboutadverse drug experience reporting for animaldrugs, contact FDA at 1-888-FDA-VETS or http://www.fda.gov/reportanimalae.

Storage

Store at controlled room temperature 20° to 25° C (68° to 77° F).

ANTIROBE AQUADROPS
Distributed by:
Zoetis Inc.
Kalamazoo, MI 49007
ANTIROBE Capsules
Manufactured for:
Zoetis Inc. by Patheon Inc.
Whitby, Canada
Distributed by:
Zoetis Inc.
Kalamazoo, MI 49007
Product of China
Revised: September 2022
40040699